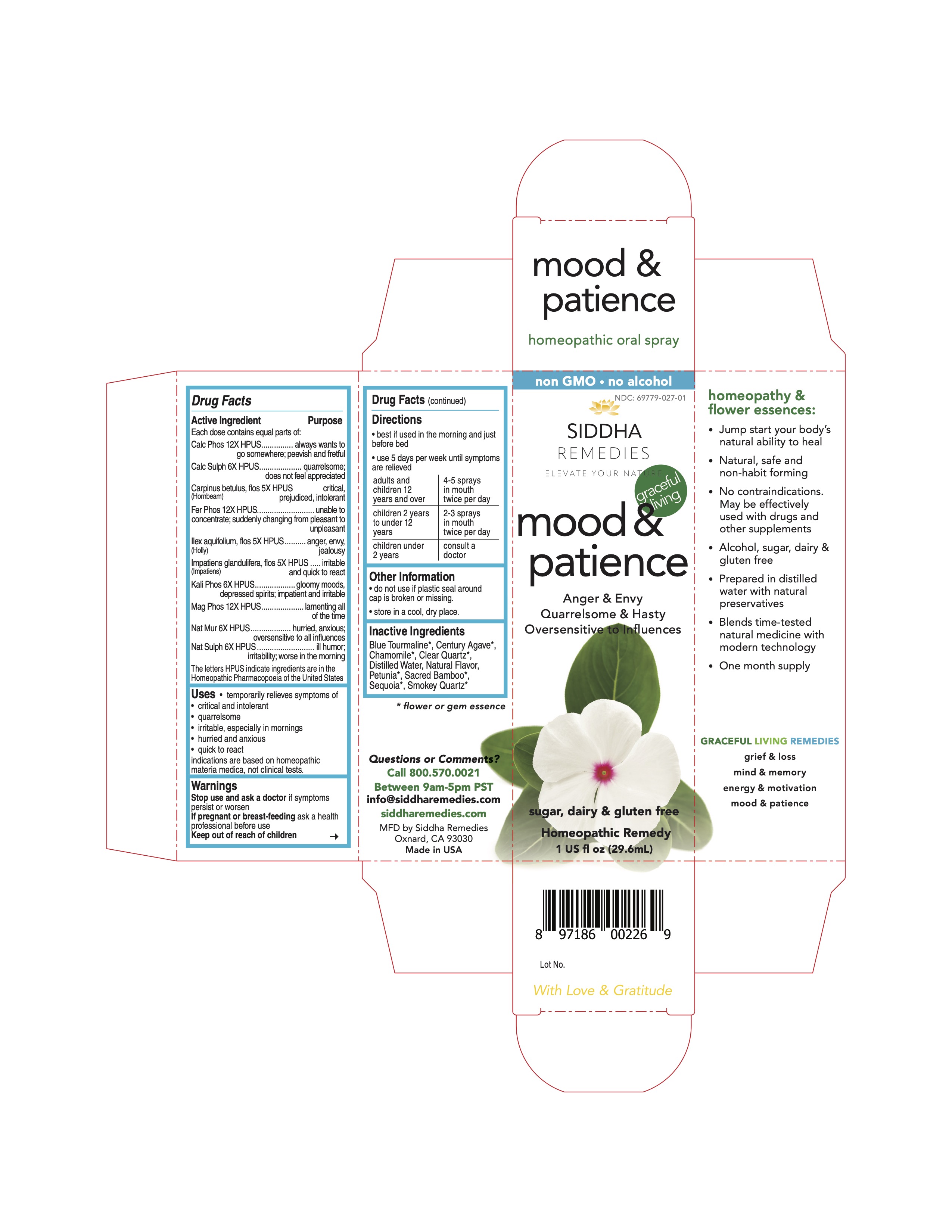 DRUG LABEL: mood and patience
NDC: 69779-027 | Form: SPRAY
Manufacturer: Siddha Flower Essences LLC
Category: homeopathic | Type: HUMAN OTC DRUG LABEL
Date: 20251231

ACTIVE INGREDIENTS: TRIBASIC CALCIUM PHOSPHATE 12 [hp_X]/29.6 mL; CALCIUM SULFATE ANHYDROUS 6 [hp_X]/29.6 mL; CARPINUS BETULUS FLOWERING TOP 5 [hp_X]/29.6 mL; FERROSOFERRIC PHOSPHATE 12 [hp_X]/29.6 mL; ILEX AQUIFOLIUM FLOWERING TOP 5 [hp_X]/29.6 mL; IMPATIENS GLANDULIFERA FLOWER 5 [hp_X]/29.6 mL; DIBASIC POTASSIUM PHOSPHATE 6 [hp_X]/29.6 mL; MAGNESIUM PHOSPHATE, DIBASIC TRIHYDRATE 12 [hp_X]/29.6 mL; SODIUM CHLORIDE 6 [hp_X]/29.6 mL; SODIUM SULFATE 6 [hp_X]/29.6 mL
INACTIVE INGREDIENTS: CHAMAEMELUM NOBILE FLOWER; AGAVE AMERICANA WHOLE; PETUNIA AXILLARIS WHOLE; WATER; NANDINA DOMESTICA WHOLE; SEQUOIA SEMPERVIRENS WHOLE

Active Ingredient

Each dose contains equal parts of:

Calc Phos 12X HPUS

Calc Sulph 6X HPUS

Carpinus betulus, flos (Hornbeam) 5X HPUS

Fer Phos 12X HPUS

Ilex aquifolium, flos (Holly) 5X HPUS

Impatiens glandulifera, flos (Impatiens) 5X HPUS

Kali Phos 6X HPUS

Mag Phos 12X HPUS

Nat Mur 6X HPUS

Nat Sulph 6X HPUS

Purpose

Each dose contains equal parts of:

Calc Phos 12X HPUS.............................................always wants to go somewhere; peevish and fretful

Calc Sulph 6X HPUS.............................................quarrelsome; does not feel appreciated

Carpinus betulus, flos (Hornbeam) 5X HPUS............critical, prejudiced, intolerant

Fer Phos 12X HPUS..............................................unable to concentrate; suddently changing from pleasant to unpleasant

Ilex aquifolium, flos (Holly) 5X HPUS......................anger, envy, jealousy

Impatiens glandulifera, flos (Impatiens) 5X HPUS....irritable and quick to react

Kali Phos 6X HPUS..............................................gloomy moods, depressed spirits; impatient and irritable

Mag Phos 12X HPUS............................................lamenting all of the time

Nat Mur 6X HPUS................................................hurried, anxious; oversensitive to all influences

Nat Sulph 6X HPUS.............................................ill humor; irritability; worse in the morning

Uses

temporarily relieves symptoms of

- critical and intolerant
- quarrelsome
- irritable, especially in mornings
- hurried and anxious
- quick to react

indications are based on homeopathic materia medica, not clinical tests.

Uses

Stop use and ask a doctor if symptoms persist or worsen

PREGNANCY OR BREAST FEEDING

If pregnant or breast-feeding ask a health professional before use

Keep out of reach of children

Directions

- best if used in the morning and just before bed
- use 5 days per week until symptoms are relieved

adults and children 12 years and over | 4-5 sprays in mouth twice per day
children 2 years to under 12 years | 2-3 sprays in mouth twice per day
children under 2 years | consult a doctor

Other Information

- do not use if plastic seal around cap is broken or missing.
- store in a cool, dry place.

Inactive Ingredients

Blue Tourmaline*, Chamomile*, Century Agave*, Clear Quartz*, Natural Flavor, Petunia*, Purified Water, Sacred Bamboo*, Sequoia*, Smokey Quartz*

*flower or gem essence

Questions or Comments?
Call 800.570.0021
Between 9am-5pm PST
info@siddhaflowers.com
siddhaflowers.com
MFD by Siddha Flower Essences
Oxnard, CA 93030
Made in USA

Side Panel

homeopathy and flower essences:

- Jump start your body's natural ability to heal
- Natural, safe and non-habit forming
- No contraindications. May be effectively used with drugs and other supplements
- Alcohol, sugar, dairy and gluten free
- Prepared in purified water with natural preservatives
- Blends time-tested natural medicine with modern technology
- One month supply

GRACEFUL AGING REMEDIES

grief & loss

mind & memory

energy & motivation

mood & patience

Principal Display Panel

non GMO - no alcohol
siddha cell salts + flower essences
mood & patience

Anger & Envy

Quarrelsome & Hasty

Oversensitive to Influences

sugar, dairy & gluten free
Homeopathic Remedy
1 US fl oz (29.6mL)